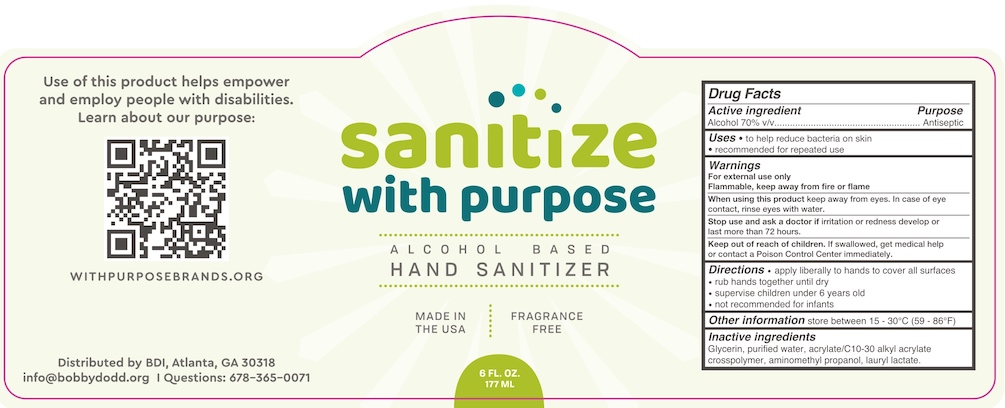 DRUG LABEL: Sanitize with Purpose
NDC: 80225-001 | Form: GEL
Manufacturer: Bobby Dodd Institute
Category: otc | Type: HUMAN OTC DRUG LABEL
Date: 20210122

ACTIVE INGREDIENTS: ALCOHOL 70 mL/100 mL
INACTIVE INGREDIENTS: AMINOMETHYLPROPANOL; GLYCERIN; WATER; CARBOMER INTERPOLYMER TYPE A (55000 CPS); LAURYL LACTATE

BDI Sanitize with Purpose

Drug Facts

Active ingredient

Alcohol 70% v/v

Purpose

Antiseptic

Uses

- to help reduce bacteria on skin
- recommended for repeated use

Warnings

For external use only

Flammable, keep away from fire or flame

When using this product keep away from eyes. In case of eye contact, rinse eyes with water.

Stop use and ask a doctor if irritation or redness develop or last more than 72 hours.

Keep out of reach of children. If swallowed, get medical help or contact a Poison Control Center immediately.

Directions

- apply liberally to hands to cover all surfaces
- rub hands together until dry
- supervise children under 6 years old
- not recommended for infants

Other information

store between 15 - 30°C (59 -86°F)

Inactive ingredients

Glycerin, purified water, acrylate/C10-30 alkyl acrylate crosspolymer, aminomethyl propanol, lauryl lactate.

Distributed by BDI, Atlanta, GA 30318

info@bobbydodd.org

Questions: 678-365-0071

PACKAGE LABEL

Sanitize with Purpose

ALCOHOL BASED

HAND SANITIZER

MADE IN THE USA | FRAGRANCE FREE

6 FL. OZ.

177 ML